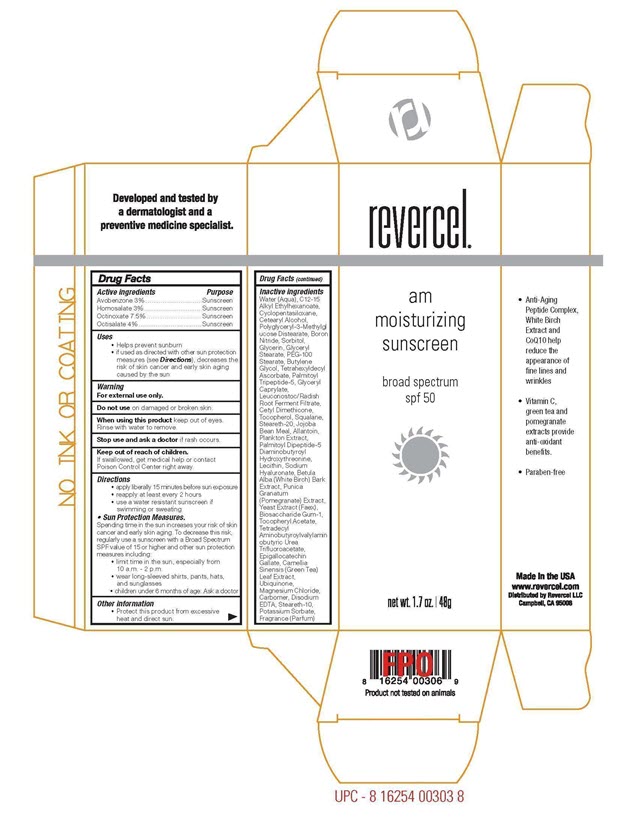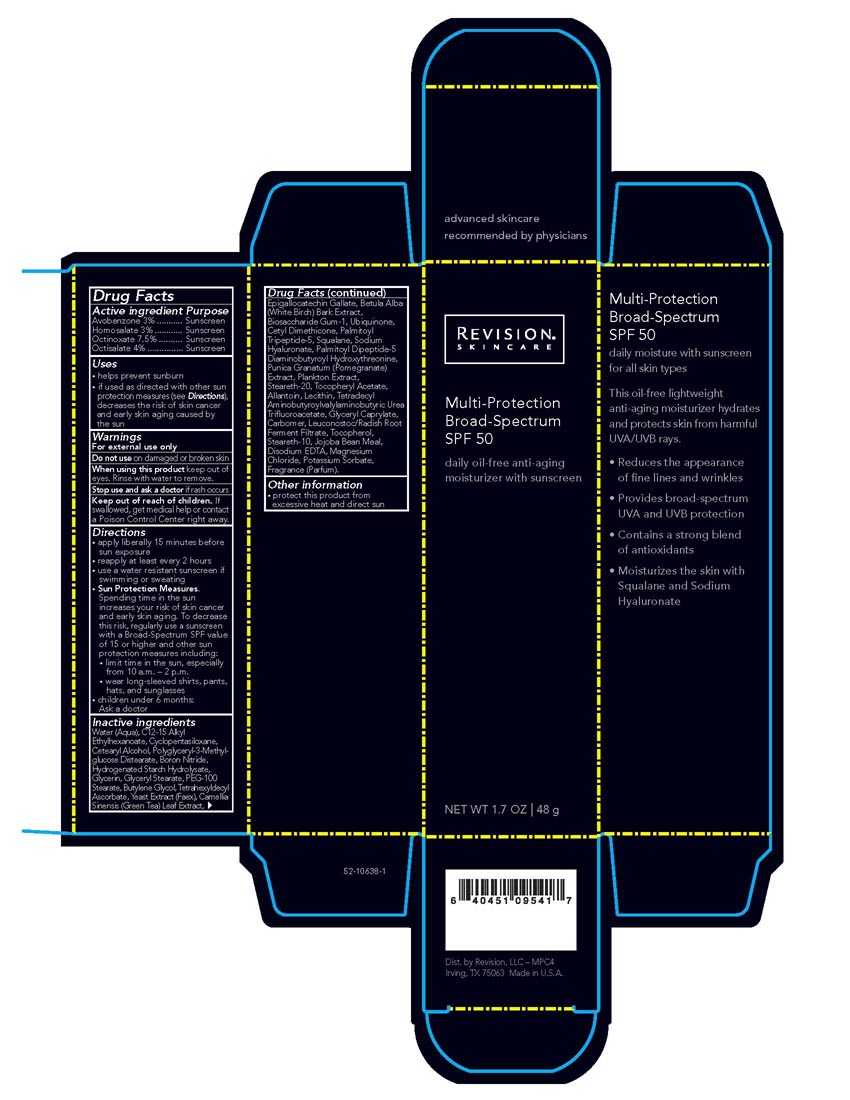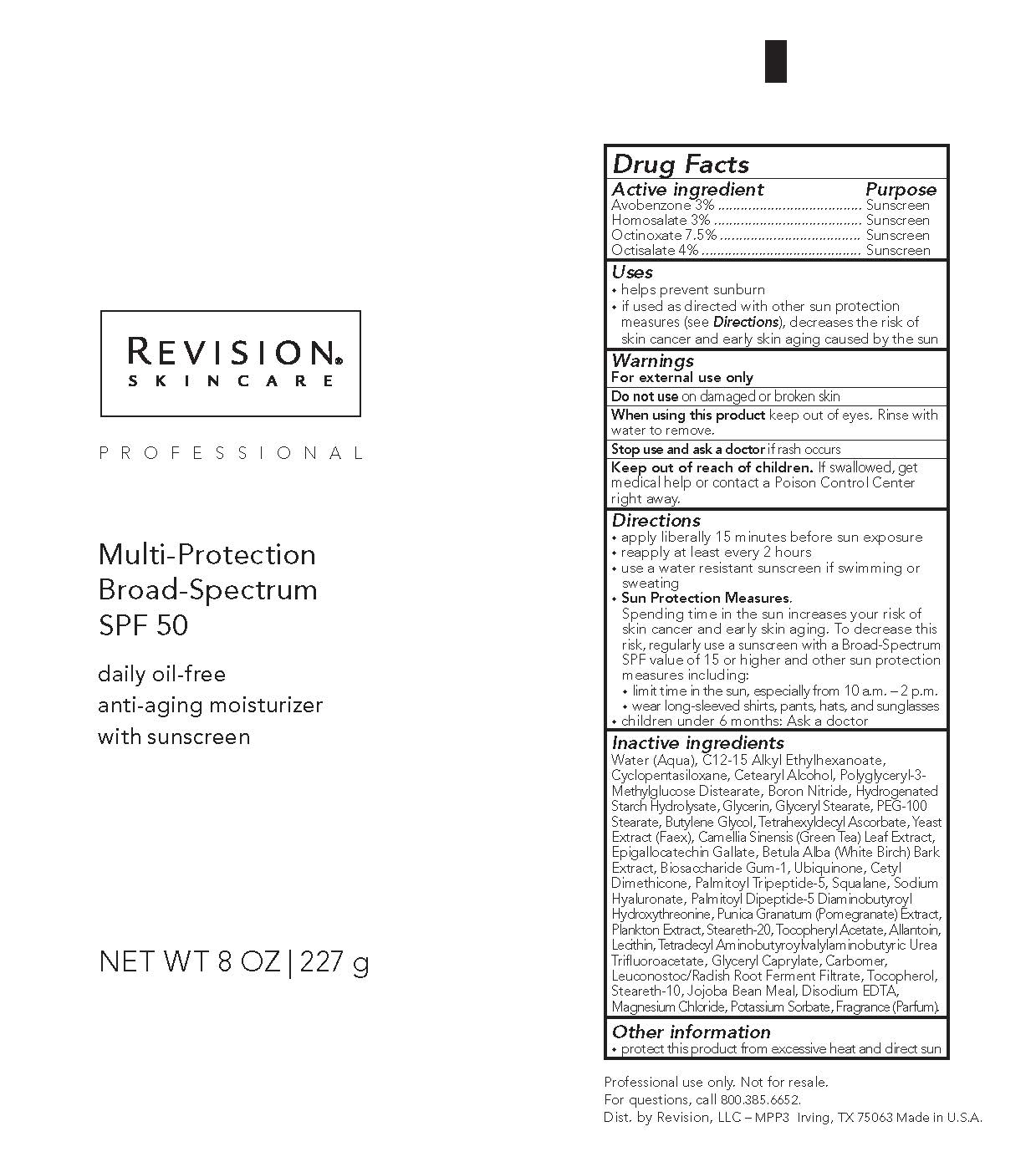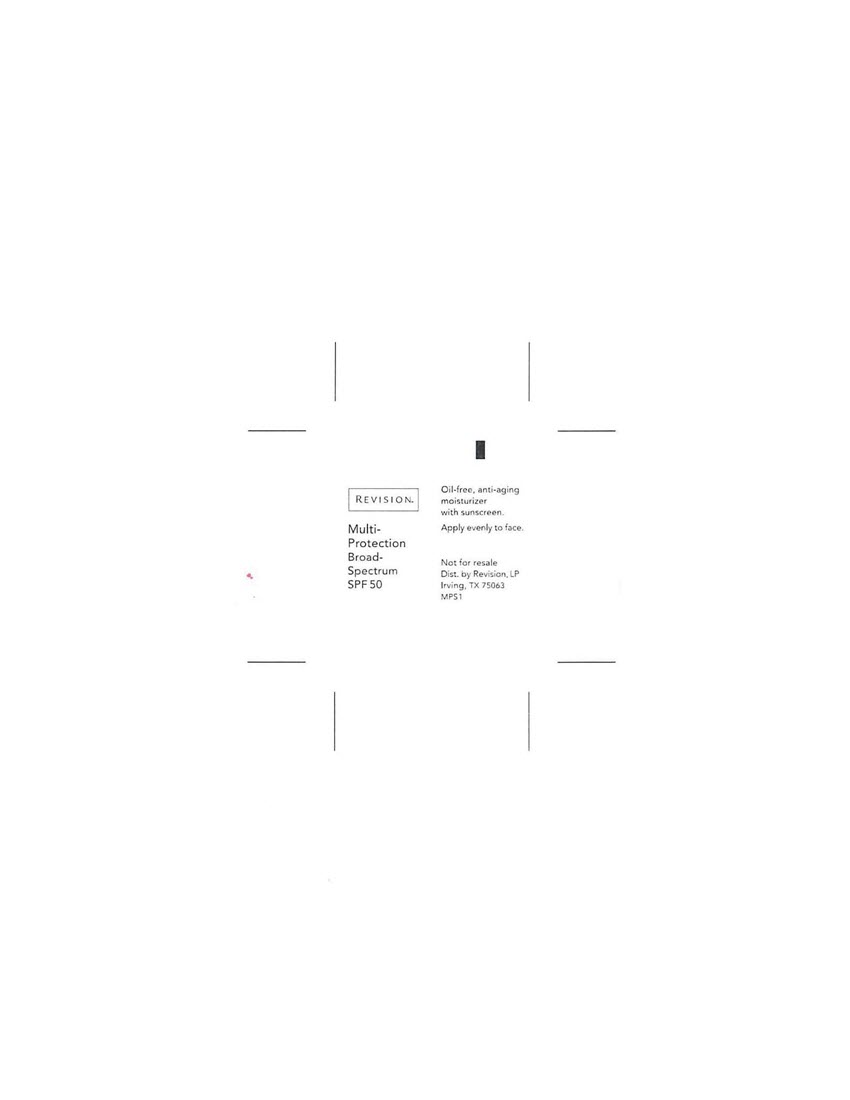 DRUG LABEL: Daily Moisturizing Antioxidant SPF 50
NDC: 10477-7720 | Form: CREAM
Manufacturer: Goodier Cosmetics LLC
Category: otc | Type: HUMAN OTC DRUG LABEL
Date: 20211019

ACTIVE INGREDIENTS: AVOBENZONE 3 g/100 g; HOMOSALATE 3 g/100 g; OCTINOXATE 7.5 g/100 g; OCTISALATE 4 g/100 g
INACTIVE INGREDIENTS: WATER; CYCLOMETHICONE 5; CETOSTEARYL ALCOHOL; BORON NITRIDE; SORBITOL; GLYCERIN; GLYCERYL MONOSTEARATE; PEG-100 STEARATE; BUTYLENE GLYCOL; TETRAHEXYLDECYL ASCORBATE; YEAST; GREEN TEA LEAF; EPIGALLOCATECHIN GALLATE; BETULA PUBESCENS BARK; BIOSACCHARIDE GUM-1; UBIDECARENONE; CETYL DIMETHICONE 25; PALMITOYL TRIPEPTIDE-5; SQUALANE; HYALURONATE SODIUM; PALMITOYLLYSYLVALYLDIAMINOBUTYROYLTHREONINE; POMEGRANATE; STEARETH-20; .ALPHA.-TOCOPHEROL ACETATE; ALLANTOIN; LECITHIN, SOYBEAN; GLYCERYL CAPRYLATE; CARBOMER INTERPOLYMER TYPE A (ALLYL SUCROSE CROSSLINKED); TOCOPHEROL; STEARETH-10; SIMMONDSIA CHINENSIS SEED; EDETATE DISODIUM; MAGNESIUM CHLORIDE; POTASSIUM SORBATE

Daily Moisturizing Antioxidant SPF 50

Revision Multi-Protection Broad-Spectrum SPF 50

Multi-Protection
Broad-Spectrum
SPF 50

daily oil-free anti-aging
moisturizer with sunscreen

NET WT 1.7 OZ | 48 g

Active ingredient Purpose

Avobenzone 3% ........... Sunscreen
Homosalate 3% ............ Sunscreen
Octinoxate 7.5% .......... Sunscreen
Octisalate 4% ............... Sunscreen

Uses

• helps prevent sunburn
• if used as directed with other sun protection measures (see Directions), decreases the risk of skin cancer and early skin aging caused by the sun

Warnings

For external use only

Do not use on damaged or broken skin

When using this product keep out of eyes. Rinse with water to remove.

Stop use and ask a doctor if rash occurs

Keep out of reach of children. If swallowed, get medical help or contact a Poison Control Center right away.

Directions
• apply liberally 15 minutes before sun exposure
• reapply at least every 2 hours
• use a water resistant sunscreen if swimming or sweating
• Sun Protection Measures.
Spending time in the sun increases your risk of skin cancer and early skin aging. To decrease this risk, regularly use a sunscreen
with a Broad-Spectrum SPF value of 15 or higher and other sun protection measures including:
• limit time in the sun, especially from 10 a.m. – 2 p.m.
• wear long-sleeved shirts, pants, hats, and sunglasses
• children under 6 months: Ask a doctor

INACTIVE INGREDIENT

Inactive ingredientsWater (Aqua), C12-15 Alkyl Ethylhexanoate, Cyclopentasiloxane, Cetearyl Alcohol, Polyglyceryl-3-Methylglucose Distearate, Boron Nitride,
Hydrogenated Starch Hydrolysate, Glycerin, Glyceryl Stearate, PEG-100 Stearate, Butylene Glycol, Tetrahexyldecyl Ascorbate, Yeast Extract
(Faex), Camellia Sinensis (Green Tea) Leaf Extract, Epigallocatechin Gallate, Betula Alba (White Birch) Bark Extract, Biosaccharide Gum-1,
Ubiquinone, Cetyl Dimethicone, Palmitoyl Tripeptide-5, Squalane, Sodium Hyaluronate, Palmitoyl Dipeptide-5 Diaminobutyroyl
Hydroxythreonine, Punica Granatum (Pomegranate) Extract, Plankton Extract, Steareth-20, Tocopheryl Acetate, Allantoin, Lecithin,
Tetradecyl Aminobutyroylvalylaminobutyric Urea Trifluoroacetate, Glyceryl Caprylate, Carbomer, Leuconostoc/Radish Root Ferment Filtrate,
Tocopherol, Steareth-10, Jojoba Bean Meal, Disodium EDTA, Magnesium Chloride, Potassium Sorbate, Fragrance (Parfum).

Other information
• protect this product from excessive heat and direct sun

Dist. by Revision, LP
Irving, TX 75063 Made in U.S.A.

Revercel AM Moisturizing Sunscreen Broad Spectrum SPF 50

am
moisturizing
sunscreen

broad spectrum
spf 50

net wt. 1.7oz. | 48g

Active ingredient Purpose
Avobenzone 3% ........... Sunscreen
Homosalate 3% ............ Sunscreen
Octinoxate 7.5% .......... Sunscreen
Octisalate 4% ............... Sunscreen

Uses
• helps prevent sunburn
• if used as directed with other sun protection measures (see Directions), decreases the risk of skin cancer and early skin aging caused by the sun

Warnings

For external use only

Do not use on damaged or broken skin

When using this product keep out of eyes. Rinse with water to remove.

Stop use and ask a doctor if rash occurs

Keep out of reach of children. If swallowed, get medical help or contact a Poison Control Center right away.

Directions
• apply liberally 15 minutes before sun exposure
• reapply at least every 2 hours
• use a water resistant sunscreen if swimming or sweating
• Sun Protection Measures.
Spending time in the sun increases your risk of skin cancer and early skin aging. To decrease this risk, regularly use a sunscreen
with a Broad-Spectrum SPF value of 15 or higher and other sun protection measures including:
• limit time in the sun, especially from 10 a.m. – 2 p.m.
• wear long-sleeved shirts, pants, hats, and sunglasses
• children under 6 months: Ask a doctor

Inactive ingredients
Water (Aqua), C12-15 Alkyl Ethylhexanoate, Cyclopentasiloxane, Cetearyl Alcohol, Polyglyceryl-3-Methylglucose Distearate,
Boron Nitride, Sorbitol, Glycerin, Glyceryl Stearate, PEG-100 Stearate, Butylene Glycol, Tetrahexyldecyl Ascorbate, Palmitoyl
Tripeptide-5, Glyceryl Caprylate, Leuconostoc/Radish Root Ferment Filtrate, Cetyl Dimethicone, Tocopherol, Squalane,
Steareth-20, Jojoba Bean Meal, Allantoin, Plankton Extract, Palmitoyl Dipeptide-5 Diaminobutyroyl Hydroxythreonine, Lecithin,
Sodium Hyaluronate, Betula Alba (White Birch) Bark Extract, Punica Granatum (Pomegranate) Extract, Yeast Extract (Faex),
Biosaccharide Gum-1, Tocopheryl Acetate, Tetradecyl Aminobutyroylvalylaminobutyric Urea Trifluoroacetate, Epigallocatechin
Gallate, Camellia Sinensis (Green Tea) Leaf Extract, Ubiquinone, Magnesium Chloride, Carbomer, Disodium EDTA, Steareth-10,
Potassium Sorbate, Fragrance (Parfum)

Other information
• protect this product from excessive heat and direct sun

Made in the USA
Distributed by Revercel LLC
Campbel, CA 95008

PACKAGE LABEL

1.7oz MPC

8oz MPC

3g MPC

1.7oz AM